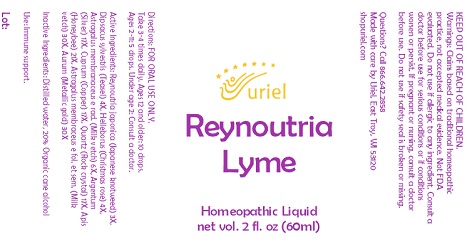 DRUG LABEL: Reynoutria Lyme
NDC: 48951-8396 | Form: LIQUID
Manufacturer: Uriel Pharmacy, Inc.
Category: homeopathic | Type: HUMAN OTC DRUG LABEL
Date: 20221011

ACTIVE INGREDIENTS: COPPER 17 [hp_X]/1 mL; SILICON DIOXIDE 17 [hp_X]/1 mL; APIS MELLIFERA 21 [hp_X]/1 mL; ASTRAGALUS CHINENSIS SEED 30 [hp_X]/1 mL; GOLD 30 [hp_X]/1 mL; SILVER 17 [hp_X]/1 mL; HELLEBORUS NIGER ROOT 4 [hp_X]/1 mL; DIPSACUS FULLONUM WHOLE 4 [hp_X]/1 mL; ASTRAGALUS PROPINQUUS ROOT 6 [hp_X]/1 mL; REYNOUTRIA JAPONICA LEAF 3 [hp_X]/1 mL
INACTIVE INGREDIENTS: WATER; ALCOHOL

Reynoutria Lyme

INDICATIONS AND USAGE

Directions: FOR ORAL USE ONLY.

DOSAGE AND ADMINISTRATION

Take 3-4 times daily. Ages 12 and older: 10 drops. Ages 2-11: 5 drops. Under age 2: Consult a doctor.

ACTIVE INGREDIENT

Active Ingredients: Reynoutria japonica (Japanese knotweed) 3X, Dipsacus sylvestris (Teasel) 4X, Helleborus (Christmas rose) 4X,
Astragalus membranaceus e rad. (Milk vetch) 6X, Argentum (Silver) 17X, Cuprum (Copper) 17X, Quartz (Rock crystal) 17X, Apis (Honeybee) 21X, Astragalus membraceus e fol. et sem. (Milk vetch) 30X, Aurum (Metallic gold) 30X

Inactive Ingredients: Distilled water, 20% Organic cane alcohol

PURPOSE

Use: Immune support.

KEEP OUT OF REACH OF CHILDREN.

WARNINGS

Warnings: Claims based on traditional homeopathic practice, not accepted medical evidence. Not FDA evaluated. Do not use if allergic to any ingredient. Consult a doctor before use for serious conditions or if conditions worsen or persist. If pregnant or nursing, consult a doctor before use. Do not use if safety seal is broken or missing.

Questions? Call 866.642.2858
Made with care by Uriel, East Troy, WI 53120
shopuriel.com Lot: